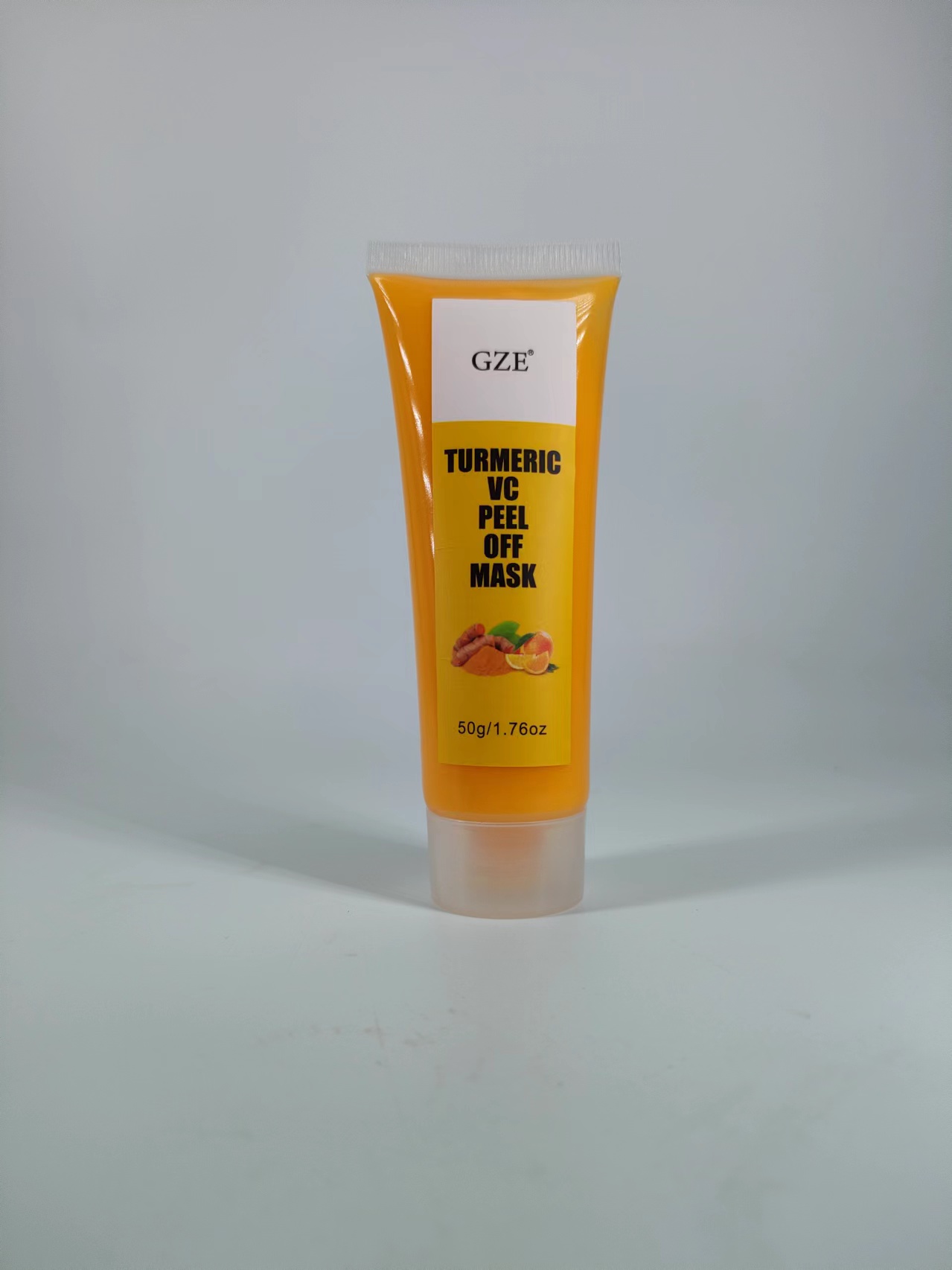 DRUG LABEL: GZE TURMERIC VC PEEL OFF MASK
NDC: 74458-268 | Form: CREAM
Manufacturer: Guangzhou Yilong Cosmetics Co., Ltd
Category: otc | Type: HUMAN OTC DRUG LABEL
Date: 20241107

ACTIVE INGREDIENTS: ASCORBIC ACID 5 g/100 g
INACTIVE INGREDIENTS: AQUA; GLYCERIN; CURCUMA LONGA (TURMERIC) ROOT EXTRACT; CITRIC ACID MONOHYDRATE; SODIUM CHLORIDE

GZE TURMERIC VC PEEL OFF MASK

PURPOSE

Exfoliation.

INACTIVE INGREDIENT

Aqua

Glycerin

Curcuma Longa (Turmeric) Root Extract

Sodium chloride

Citric Acid

Fragrance

WARNINGS

For external use only.

Stop use and ask a doctor if rash occurs.

INDICATIONS AND USAGE

Apply a thick, even layer of the peel-off mask to your face. Allow the mask to dry for 15-20 minutes, gently peel off the mask starting from the edges. Rinse your face with warm water.

Do not use on damaged or broken skin.

When using this product keep out of eyes. Rinse with water to remove.

Keep out of reach of children. If swallowed, get medical help or contact a Poison Control Center right away.

DOSAGE AND ADMINISTRATION

Apply a thick, even layer of the peel-off mask to your face. Allow the mask to dry for 15-20 minutes, gently peel off the mask starting from the edges. Rinse your face with warm water.